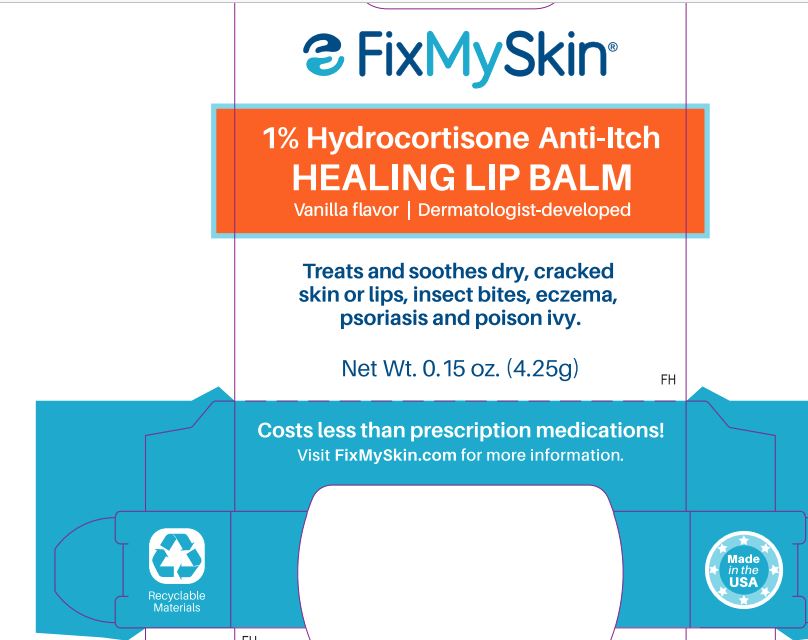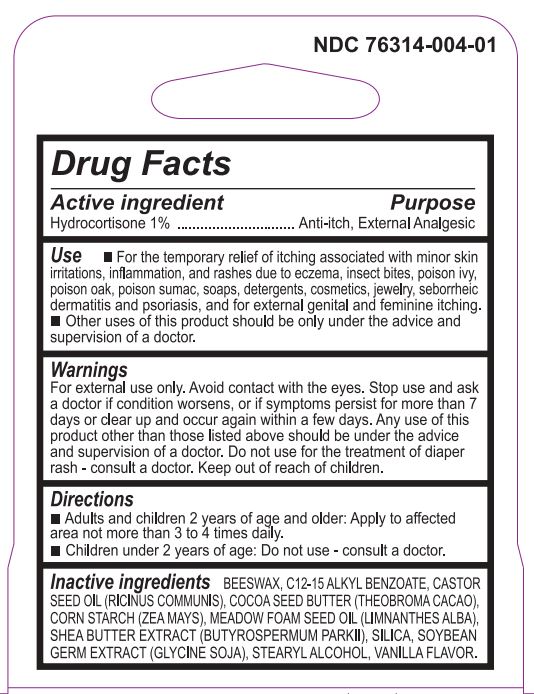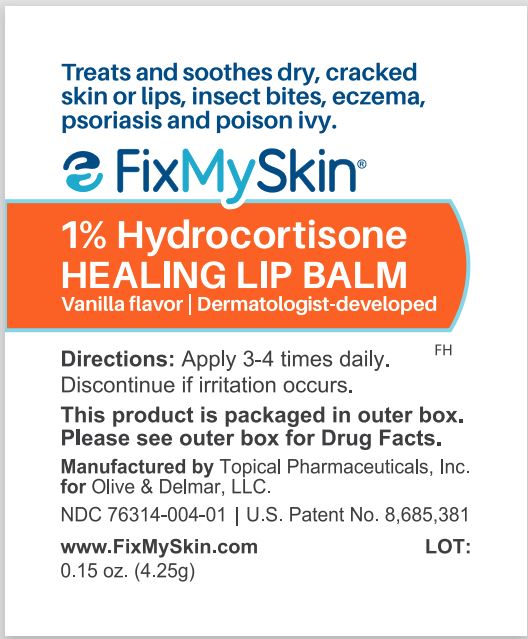 DRUG LABEL: FixMySkin Healing Balm Vanilla Flavor
NDC: 76314-004 | Form: OINTMENT
Manufacturer: Lovely Skin, Inc.
Category: otc | Type: HUMAN OTC DRUG LABEL
Date: 20241231

ACTIVE INGREDIENTS: HYDROCORTISONE 10 mg/1 mL
INACTIVE INGREDIENTS: CASTOR OIL; STEARYL ALCOHOL; ALKYL (C12-15) BENZOATE; MEADOWFOAM SEED OIL; SHEANUT OIL; YELLOW WAX; SOYBEAN; STARCH, CORN; SILICON DIOXIDE; COCOA BUTTER; VANILLA

FixMySkin Healing Balm Vanilla Flavor

Active Ingredient Purpose Hydrocortisone 1% ..................................................................Antipruritic, External Analgesic

Uses

For the temporary relief of itching associated with minor skin irritations, inflammation, and rashes due to eczema, psoriasis, seborrheic dermatitis, insect bites, poison oak, or poison sumac, soaps, detergents, cosmetics, and jewelry, and for external genital and feminine itching, and external analgesic. Other uses of this product should only be under the advice and supervision of a doctor.

Warnings

For external use only. Avoid contact with eyes.

Stop use

and ask a doctor if condition worsens, or if symptoms persist for more than 7 days or clear up and occur again within a few days. Any use of this product other than those listed above should be under the advice and supervision of a doctor.

Do not use

for the treatment of diaper rash. Consult a doctor.

Keep out of reach of children

Directions

For itching associated with skin irritation, inflammation and rashes: Adults and children 2 years of age and older: apply to the affected area not more than 3 to 4 times daily. Children under 2 years of age: do not use - consult a doctor.

Inactive Ingredients

Ricinus Communis (Castor) Seed Oil, Stearyl Alcohol, C12-15 Alkyl Benzoate, Meadow Foam (Limnanthes Alba) Seed Oil, Shea Butter (Butyrospermum Parkil) Extract, Beeswax, Glycine Soja (Soybean) Germ Extract, Zea Mays (Corn) Starch, Silica, Theobroma Cacao (Cocoa) Seed Butter, Vanilla Flavor.

Questions or Comments?

www.FixMySkin.com Info@FixMySkin.com (402)697-1100

Description

Formulated by a board-certified dermatologist and his son. Dr. Joel Schlessinger and his son, Daniel Schlessinger, embarked on a five year quest to find the best balm product in a stick formulation for dry skin and irritation. After 54 different formulas, they finally came up with this patent pending formula. It is great for dry skin and helps improve the signs and symptoms of dry skin due to eczema, medications, psoriasis and other dry skin conditions. It is also available in the LovelySkin line without hydrocortisone (www.LovelySkin.com/Balm). Visit www.FixMySkin.com/Story for the whole story on how this product was developed.

Purpose

Antipruritic, External Analgesic